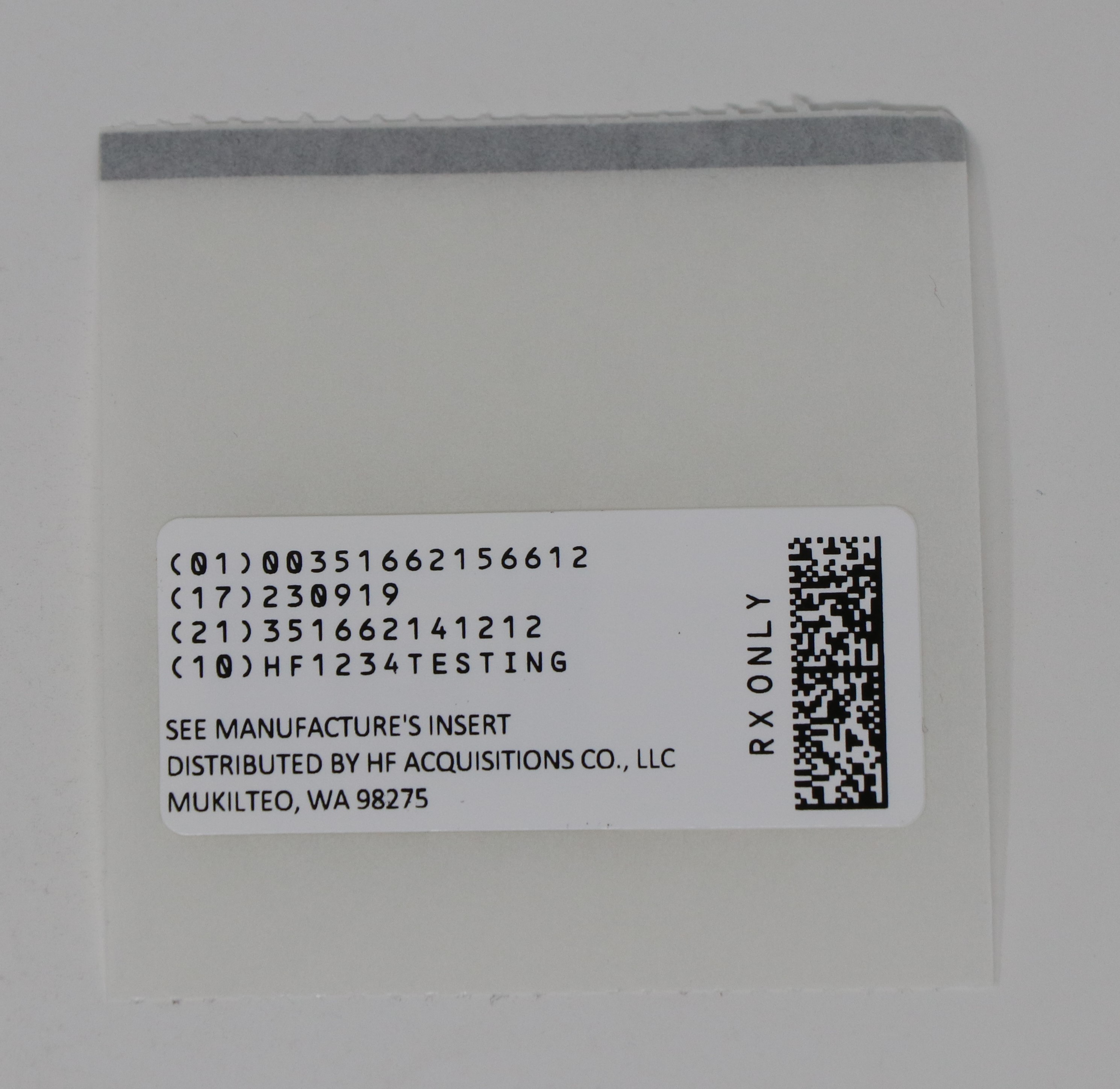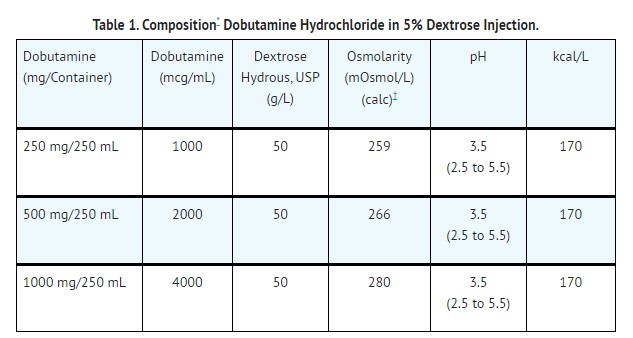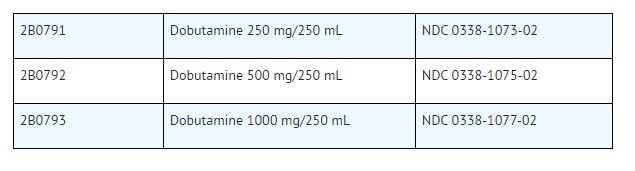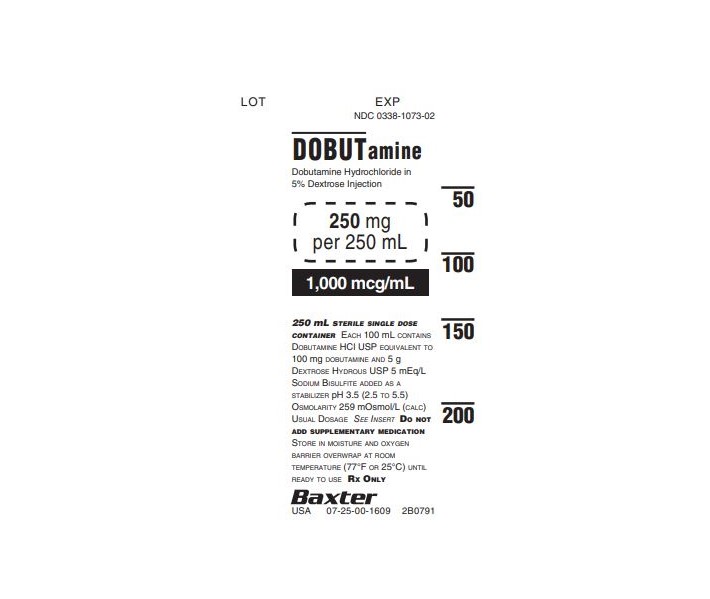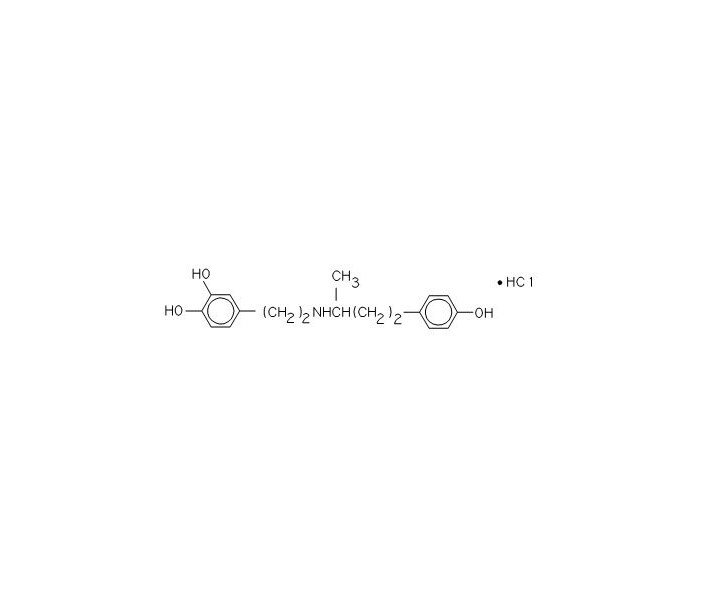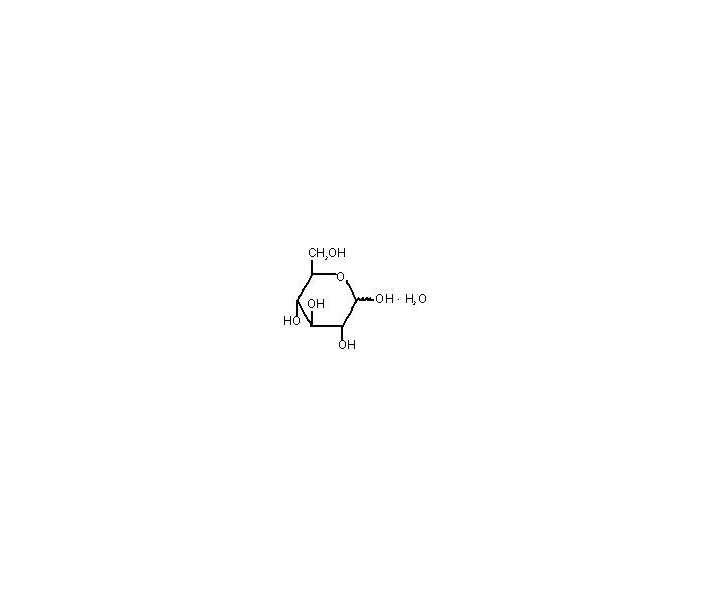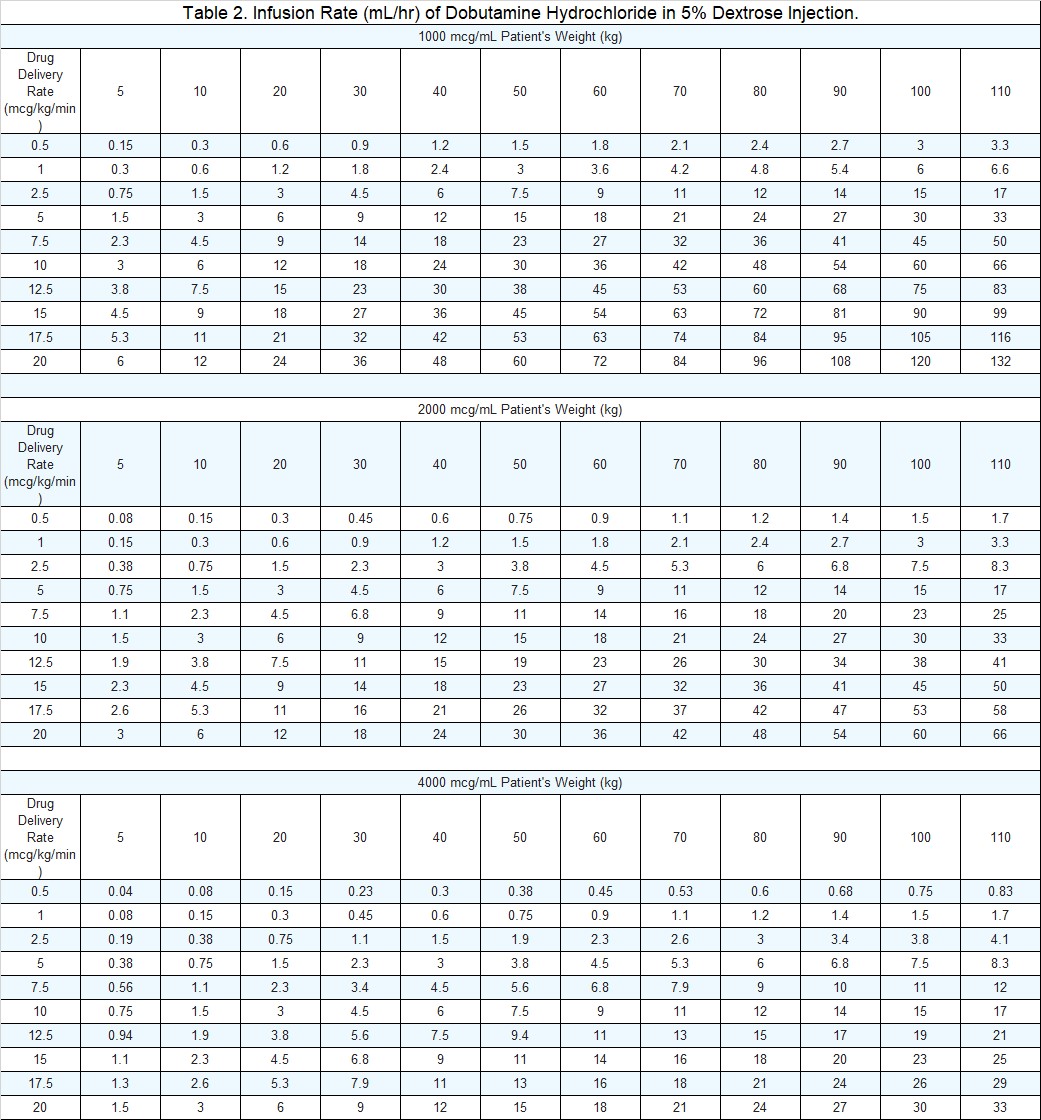 DRUG LABEL: DOBUTAMINE HYDROCHLORIDE
NDC: 51662-1566 | Form: INJECTION
Manufacturer: HF Acquisition Co LLC, DBA HealthFirst
Category: prescription | Type: HUMAN PRESCRIPTION DRUG LABEL
Date: 20240130

ACTIVE INGREDIENTS: DOBUTAMINE HYDROCHLORIDE 100 mg/100 mL
INACTIVE INGREDIENTS: HYDROCHLORIC ACID; DEXTROSE MONOHYDRATE 5 g/100 mL; SODIUM BISULFITE 0.5 meq/100 mL; SODIUM HYDROXIDE; WATER

DOBUTAMINE HYDROCHLORIDE IN 5% DEXTROSE INJECTION, 250mg PER 250mL (1,000 mcg/mL)

DESCRIPTION

Dobutamine Hydrochloride in 5% Dextrose Injection is a sterile, nonpyrogenic solution of Dobutamine Hydrochloride, USP and Dextrose, USP in Water for Injection, USP. Dobutamine hydrochloride is chemically designated as (±)-4-[2-[[3-(p-hydroxyphenyl)-1-methylpropyl]amino]ethyl]-pyrocatechol hydrochloride. It is a synthetic catecholamine. Dextrose Hydrous, USP is chemically designated as D-Glucopyranose monohydrate. Structural formulas are shown below:

Dobutamine Hydrochloride, USP

(D-Glucopyranose monohydrate) Dextrose Hydrous, USP

Dobutamine Hydrochloride in 5% Dextrose Injection is intended for intravenous use only. It contains no antimicrobial agents. The pH is adjusted with sodium hydroxide and/or hydrochloric acid. Sodium bisulfite is added as a stabilizer. The solution is intended for single use only. When smaller doses are required, the unused portion should be discarded. Composition, osmolarity, pH and caloric content are given in Table 1.

*
Approximately 5 mEq/L sodium bisulfite is added as a stabilizer.
†
Normal physiologic osmolarity range is approximately 280 to 310 mOsmol/L. Administration of substantially hypertonic solutions (≥ 600 mOsmol/L) may cause vein damage.

This VIAFLEX PLUS plastic container is fabricated from a specially formulated polyvinyl chloride (PL 2207 Plastic). VIAFLEX containers, including VIAFLEX PLUS containers, are made of flexible plastic and are for parenteral use. VIAFLEX PLUS on the container indicates the presence of a drug additive in a drug vehicle. The amount of water that can permeate from inside the container into the overwrap is insufficient to affect the solution significantly. Solutions in contact with the plastic container can leach out certain of its chemical components in very small amounts within the expiration period, e.g., di-2-ethylhexyl phthalate (DEHP), up to 5 parts per million; however, the safety of the plastic has been confirmed in tests in animals according to USP biological tests for plastic containers as well as by tissue culture toxicity studies.

CLINICAL PHARMACOLOGY

Dobutamine hydrochloride is a direct-acting inotropic agent whose primary activity results from stimulation of the beta-receptors of the heart while producing comparatively mild chronotropic, hypertensive, arrhythmogenic, and vasodilative effects. It does not cause the release of endogenous norepinephrine, as does dopamine. In animal studies, dobutamine produces less increase in heart rate and less decrease in peripheral vascular resistance for a given inotropic effect than does isoproterenol.

In patients with depressed cardiac function, both dobutamine and isoproterenol increase the cardiac output to a similar degree. In the case of dobutamine, this increase is usually not accompanied by marked increases in heart rate (although tachycardia is occasionally observed), and the cardiac stroke volume is usually increased. In contrast, isoproterenol increases the cardiac index primarily by increasing the heart rate while stroke volume changes little or declines.

Facilitation of atrioventricular conduction has been observed in human electrophysiologic studies and in patients with atrial fibrillation.

Systemic vascular resistance is usually decreased with administration of dobutamine. Occasionally, minimum vasoconstriction has been observed.

Most clinical experience with dobutamine is short-term - not more than several hours in duration. In the limited number of patients who were studied for 24, 48, and 72 hours, a persistent increase in cardiac output occurred in some, whereas output returned toward baseline values in others.

The onset of action of dobutamine is within one to two minutes; however, as much as ten minutes may be required to obtain the peak effect of a particular infusion rate.

The plasma half-life of dobutamine in humans is two minutes. The principal routes of metabolism are methylation of the catechol and conjugation. In human urine, the major excretion products are the conjugates of dobutamine and 3-O-methyl dobutamine. The 3-O-methyl derivative of dobutamine is inactive.

Alteration of synaptic concentrations of catecholamines with either reserpine or tricyclic antidepressants does not alter the actions of dobutamine in animals, which indicates that the actions of dobutamine are not dependent on presynaptic mechanisms.

The effective infusion rate of dobutamine varies widely from patient to patient, and titration is always necessary (see DOSAGE AND ADMINISTRATION). At least in pediatric patients, dobutamine-induced increases in cardiac output and systemic pressure are generally seen, in any given patient, at lower infusion rates than those that cause substantial tachycardia (see PRECAUTIONS, PEDIATRIC USE).

Dextrose provides a source of calories. Dextrose is readily metabolized, may decrease losses of body protein and nitrogen, promotes glycogen deposition and decreases or prevents ketosis if sufficient doses are provided.

INDICATIONS & USAGE

Dobutamine Hydrochloride in 5% Dextrose Injection is indicated when parenteral therapy is necessary for inotropic support in the short-term treatment of patients with cardiac decompensation due to depressed contractility resulting either from organic heart disease or from cardiac surgical procedures. Experience with intravenous dobutamine in controlled trials does not extend beyond 48 hours of repeated boluses and/or continuous infusions.

Whether given orally, continuously intravenously, or intermittently intravenously, neither dobutamine nor any other cyclic-AMP-dependent inotrope has been shown in controlled trials to be safe or effective in the long-term treatment of congestive heart failure. In controlled trials of chronic oral therapy with various such agents, symptoms were not consistently alleviated, and the cyclic-AMP-dependent inotropes were consistently associated with increased risks of hospitalization and death. Patients with NYHA Class IV symptoms appeared to be at particular risk.

CONTRAINDICATIONS

Dobutamine Hydrochloride in 5% Dextrose Injection is contraindicated in patients with idiopathic hypertrophic subaortic stenosis and in patients who have shown previous manifestations of hypersensitivity to dobutamine.

Solutions containing dextrose may be contraindicated in patients with known allergy to corn or corn products.

WARNINGS

Increase in Heart Rate or Blood Pressure

Dobutamine Hydrochloride in 5% Dextrose Injection may cause a marked increase in heart rate or blood pressure, especially systolic pressure. Approximately 10% of adult patients in clinical studies have had rate increases of 30 beats/minute or more, and about 7.5% have had a 50-mm Hg or greater increase in systolic pressure. Usually, reduction of dosage reverses these effects. Because dobutamine facilitates atrioventricular conduction, patients with atrial fibrillation are at risk of developing rapid ventricular response. Patients with preexisting hypertension appear to face an increased risk of developing an exaggerated pressor response. In patients who have atrial fibrillation with rapid ventricular response, a digitalis preparation should be used prior to institution of therapy with Dobutamine in D5W.

Ectopic Activity

Dobutamine Hydrochloride in 5% Dextrose Injection may precipitate or exacerbate ventricular ectopic activity, but it rarely has caused ventricular tachycardia.

Hypersensitivity

Reactions suggestive of hypersensitivity associated with administration of dobutamine including skin rash, fever, eosinophilia, and bronchospasm, have been reported occasionally.

Dobutamine Hydrochloride in 5% Dextrose Injection contains sodium bisulfite, a sulfite that may cause allergic-type reactions, including anaphylactic symptoms and life-threatening or less severe asthmatic episodes, in certain susceptible people. The overall prevalence of sulfite sensitivity in the general population is unknown and probably low. Sulfite sensitivity is seen more frequently in asthmatic than in nonasthmatic people.

Solutions containing dextrose should not be administered through the same administration set as blood, as this may result in pseudoagglutination or hemolysis.

The intravenous administration of solutions may cause fluid overloading resulting in dilution of serum electrolyte concentrations, overhydration, congested states or pulmonary edema. The risk of dilutional states is inversely proportional to the electrolyte concentrations of the injections. The risk of solute overload causing congested states with peripheral and pulmonary edema is directly proportional to the electrolyte concentration of the injections.

Excess administration of potassium-free solutions may result in significant hypokalemia.

PRECAUTIONS

General

During the administration of Dobutamine Hydrochloride in 5% Dextrose Injection, as with any adrenergic agent, ECG and blood pressure should be continuously monitored. In addition, pulmonary wedge pressure and cardiac output should be monitored whenever possible to aid in the safe and effective infusion of dobutamine.

Hypovolemia should be corrected with suitable volume expanders before treatment with dobutamine is instituted.

Animal studies indicate that dobutamine may be ineffective if the patient has recently received a beta-blocking drug. In such a case, the peripheral vascular resistance may increase.

No improvement may be observed in the presence of marked mechanical obstruction, such as severe valvular aortic stenosis.

Solutions containing dextrose should be used with caution in patients with known subclinical or overt diabetes mellitus.

Do not administer unless solution is clear and seal is intact.

If administration is controlled by a pumping device, care must be taken to discontinue pumping action before the container runs dry or air embolism may result.

Usage Following Acute Myocardial Infarction

Clinical experience with dobutamine following myocardial infarction has been insufficient to establish the safety of the drug for this use. There is concern that any agent that increases contractile force and heart rate may increase the size of an infarction by intensifying ischemia, but it is not known whether dobutamine does so.

Drug Interactions

There was no evidence of drug interactions in clinical studies in which dobutamine was administered concurrently with other drugs, including digitalis preparations, furosemide, spironolactone, lidocaine, glyceryl trinitrate, isosorbide dinitrate, morphine, atropine, heparin, protamine, potassium chloride, folic acid, and acetaminophen. Preliminary studies indicate that the concomitant use of dobutamine and nitroprusside results in a higher cardiac output and, usually, a lower pulmonary wedge pressure than when either drug is used alone.

Carcinogenesis, Mutagenesis, Impairment of Fertility

Studies to evaluate the carcinogenic or mutagenic potential of dobutamine or the potential of the drug to affect fertility adversely have not been performed.

Pregnancy

Reproduction studies performed in rats and rabbits have revealed no evidence of harm to the fetus due to dobutamine. The drug, however, has not been administered to pregnant women and should be used only when the expected benefits clearly outweigh the potential risks to the fetus.

Pediatric Use

Dobutamine has been shown to increase cardiac output and systemic pressure in pediatric patients of every age group. In premature neonates, however, dobutamine is less effective than dopamine in raising systemic blood pressure without causing undue tachycardia, and dobutamine has not been shown to provide any added benefit when given to such infants already receiving optimal infusions of dopamine.

Geriatric Use

Clinical studies of dobutamine injection did not include sufficient numbers of subjects aged 65 and over to determine whether they respond differently from younger subjects. Other reported clinical experience has not identified differences in responses between the elderly and younger patients. In general, dose selection for an elderly patient should be cautious, usually starting at the low end of the dosing range, reflecting the greater frequency of decreased hepatic, renal, or cardiac function, and of concomitant disease or drug therapy.

ADVERSE REACTIONS

Increased Heart Rate, Blood Pressure, and Ventricular Ectopic Activity

A 10 to 20-mm Hg increase in systolic blood pressure and an increase in heart rate of 5 to 15 beats/minute have been noted in most patients (see WARNINGS regarding exaggerated chronotropic and pressor effects). Approximately 5% of adult patients have had increased premature ventricular beats during infusions. These effects are dose related.

Hypotension

Precipitous decreases in blood pressure have occasionally been described in association with dobutamine therapy. Decreasing the dose or discontinuing the infusion typically results in rapid return of blood pressure to baseline values. In rare cases, however, intervention may be required and reversibility may not be immediate.

Stress Cardiomyopathy

Stress cardiomyopathy has been reported with dobutamine in association with cardiac stress testing.

Reactions at Sites of Intravenous Infusion

Phlebitis has occasionally been reported. Local inflammatory changes have been described following inadvertent infiltration.

Miscellaneous Uncommon Effects

The following adverse effects have been reported in 1% to 3% of adult patients: nausea, headache, anginal pain, nonspecific chest pain, palpitations, and shortness of breath.

Administration of dobutamine, like other catecholamines, has been associated with decreases in serum potassium concentrations, rarely to hypokalemic values.

OVERDOSAGE

Overdoses of dobutamine have been reported rarely. The following is provided to serve as a guide if such an overdose is encountered.

Signs and Symptoms

Toxicity from dobutamine is usually due to excessive cardiac beta-receptor stimulation. The duration of action of dobutamine is generally short (T1/2 = two minutes) because it is rapidly metabolized by catechol-O-methyltransferase. The symptoms of toxicity may include anorexia, nausea, vomiting, tremor, anxiety, palpitations, headache, shortness of breath, and anginal and nonspecific chest pain. The positive inotropic and chronotropic effects of dobutamine on the myocardium may cause hypertension, tachyarrhythmias, myocardial ischemia, and ventricular fibrillation. Hypotension may result from vasodilation.

If the product is ingested, unpredictable absorption may occur from the mouth and the gastrointestinal tract.

Treatment

To obtain up-to-date information about the treatment of overdose, a good resource is your certified Regional Poison Control Center. Telephone numbers of certified poison control centers are listed in the Physicians’ Desk Reference (PDR). In managing overdosage, consider the possibility of multiple drug overdoses, interaction among drugs, and unusual drug kinetics in your patient.

The initial actions to be taken in a dobutamine overdose are discontinuing administration, establishing an airway, and ensuring oxygenation and ventilation. Resuscitative measures should be initiated promptly. Severe ventricular tachyarrhythmias may be successfully treated with propranolol or lidocaine. Hypertension usually responds to a reduction in dose or discontinuation of therapy.

Protect the patient’s airway and support ventilation and perfusion. If needed, meticulously monitor and maintain, within acceptable limits, the patient’s vital signs, blood gases, serum electrolytes, etc. Absorption of drugs from the gastrointestinal tract may be decreased by giving activated charcoal, which, in many cases, is more effective than emesis or lavage; consider charcoal instead of or in addition to gastric emptying. Repeated doses of charcoal over time may hasten elimination of some drugs that have been absorbed. Safeguard the patient’s airway when employing gastric emptying or charcoal.

Forced diuresis, peritoneal dialysis, hemodialysis, or charcoal hemoperfusion have not been established as beneficial for an overdose of dobutamine.

DOSAGE & ADMINISTRATION

Recommended Dosage

Dobutamine Hydrochloride in 5% Dextrose Injection is administered intravenously through a suitable intravenous catheter or needle. A calibrated electronic infusion device is recommended for controlling the rate of flow in mL/hour or drops/minute.

Infusion of dobutamine should be started at a low rate (0.5-1.0 mcg/kg/min) and titrated at intervals of a few minutes, guided by the patient’s response, including systemic blood pressure, urine flow, frequency of ectopic activity, heart rate, and (whenever possible) measurements of cardiac output, central venous pressure, and/or pulmonary capillary wedge pressure. In reported trials, the optimal infusion rates have varied from patient to patient, usually 2-20 mcg/kg/min but sometimes slightly outside of this range. On rare occasions, infusion rates up to 40 mcg/kg/min have been required to obtain the desired effect.

Rates of infusion in mL/hour for dobutamine hydrochloride concentrations of 1,000, 2,000 and 4,000 mcg/mL are in Table 2.

This container system may be inappropriate for the dosage requirements of pediatric patients under 30 kg. Other dosage forms may be more appropriate.

Parenteral drug products should be inspected visually for particulate matter and discoloration prior to administration whenever solution and container permit.

Dobutamine Hydrochloride in 5% Dextrose Injection solutions may exhibit a pink color that, if present, will increase with time. This color change is due to slight oxidation of the drug, but there is no significant loss of potency.

The rate of administration and the duration of therapy should be adjusted according to the patient’s response, as determined by heart rate, presence of ectopic activity, blood pressure, urine flow, and, whenever possible, measurement of central venous or pulmonary wedge pressure and cardiac output.

Do not add supplementary medications to Dobutamine Hydrochloride in 5% Dextrose Injection. Do not administer Dobutamine Hydrochloride in 5% Dextrose Injection simultaneously with solutions containing sodium bicarbonate or strong alkaline solutions.

HOW SUPPLIED

Dobutamine Hydrochloride in 5% Dextrose Injection in VIAFLEX PLUS plastic containers is available as follows:

Exposure of pharmaceutical products to heat should be minimized. Avoid excessive heat. Protect from freezing. It is recommended the product be stored at room temperature (25°C); brief exposure up to 40°C does not adversely affect the product.

Directions for use of VIAFLEX PLUS Plastic Container

Do not remove unit from overwrap until ready for use.

To open

Tear overwrap down side at notch and remove solution container. Some opacity of the plastic due to moisture absorption during the sterilization process may be observed. This is normal and does not affect the solution quality or safety. The opacity will diminish gradually. Check for minute leaks by squeezing inner bag firmly. If leaks are found, discard solution as sterility may be impaired.

Preparation for Administration

Visually inspect the container. If the administration port protector is damaged, detached, or not present, discard container as solution path sterility may be impaired.

Caution: Do not use plastic containers in series connections. Such use could result in air embolism due to residual air being drawn from the primary container before administration of the fluid from the secondary container is completed.

1.
Suspend container from eyelet support.
2.
Remove plastic protector from administration port at bottom of container.
3.
Attach administration set. Refer to complete directions accompanying set.

Baxter, Viaflex and Viaflex Plus are trademarks of Baxter International Inc.

Baxter Healthcare Corporation
Deerfield, IL 60015 USA
Printed in USA

07-19-00-0594
Rev. March 2019